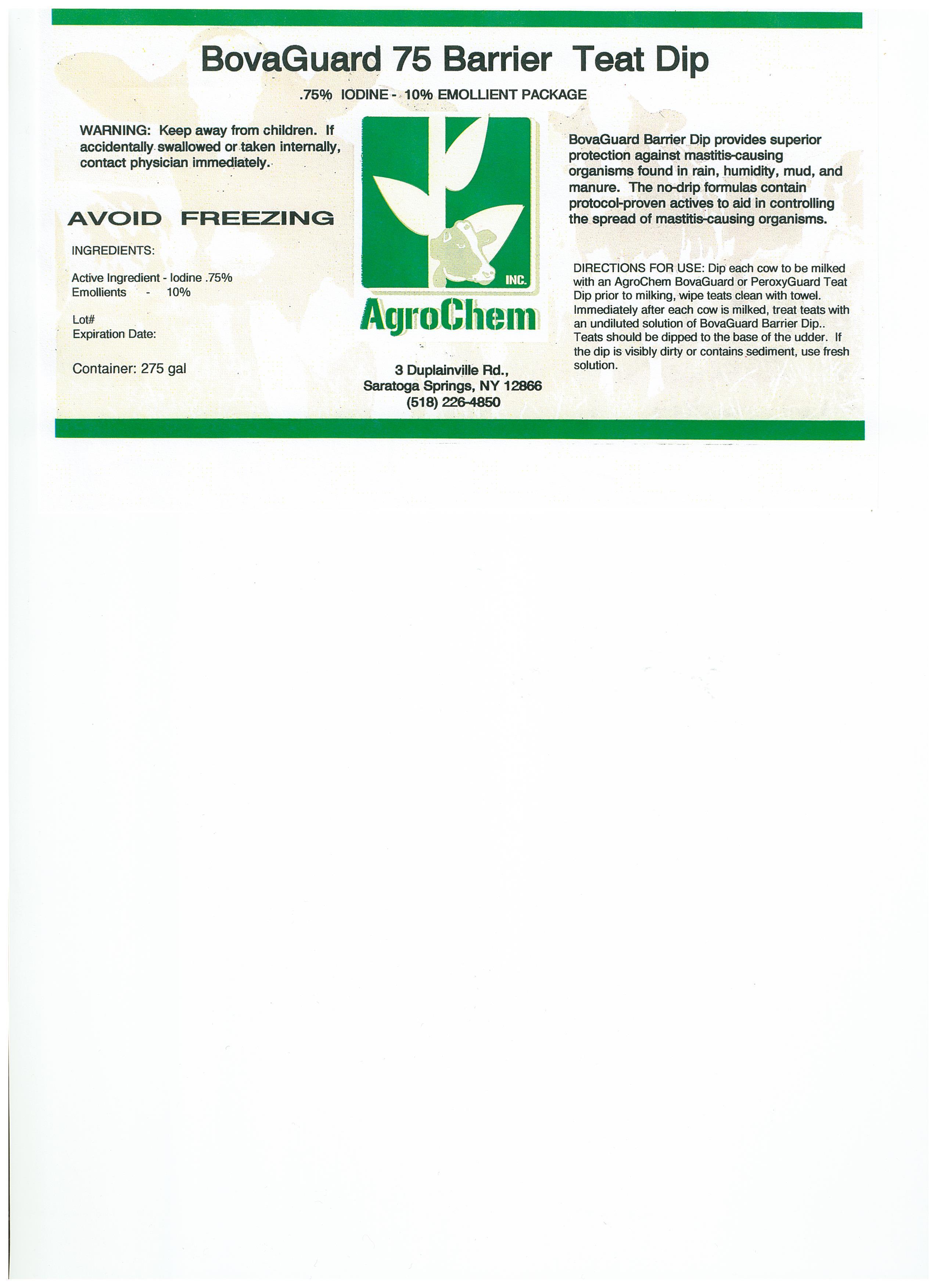 DRUG LABEL: BovaGuard 75 Barrier Teat Dip
NDC: 17307-0075 | Form: SOLUTION
Manufacturer: AgroChem Inc
Category: animal | Type: OTC ANIMAL DRUG LABEL
Date: 20130814

ACTIVE INGREDIENTS: IODINE .075 kg/1 kg
INACTIVE INGREDIENTS: WATER .849 kg/1 kg; GLYCERIN .04 kg/1 kg; ALGINIC ACID .002 kg/1 kg; PROPYLENE GLYCOL .02 kg/1 kg; 1,3-BUTYLENE GLYCOL .01 kg/1 kg; XANTHAN GUM .0037 kg/1 kg

BovaGuard 75 Barrier Teat Dip

ACTIVE INGREDIENT

.75% IODINE - 10% EMOLLIENT PACKAGE

WARNINGS

WARNING: Keep away from children. If

accidentally swallowed or taken

internally, contact physician

immediately.

AVOID FREEZING

ACTIVE INGREDIENT

INGREDIENTS:

Active Ingredient - Iodine .75%

Emollients - 10%

DESCRIPTION

BovaGuard Barrier Dip provides superior

protection against mastitis-causing

organisms found in rain, humidity, mud,

and manure. The no-drip formulas contain

protocol-proven actives to aid in controlling

the spread of mastitis-causing organisms.

INSTRUCTIONS FOR USE

DIRECTIONS FOR USE: Dip each cow to be milked

with an AgroChem BovaGuard or PeroxyGuard Teat

Dip prior to milking, wipe teats clean with towel.

Immediately after each cow is milked, treat teats with

an undiluted solution of BovaGuard Barrier Dip.

Teats should be dipped to the base of the udder. If

the dip is visibly dirty or contains sediment, use fresh

solution.